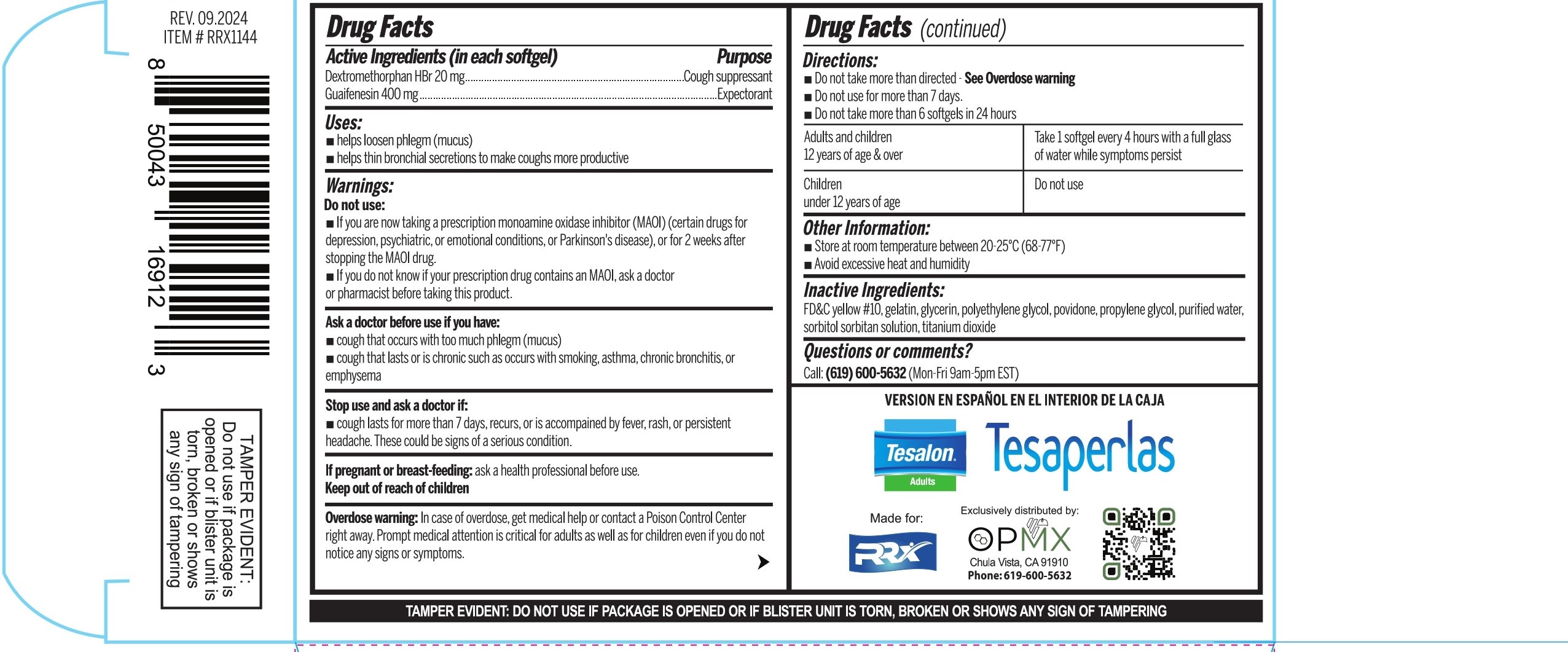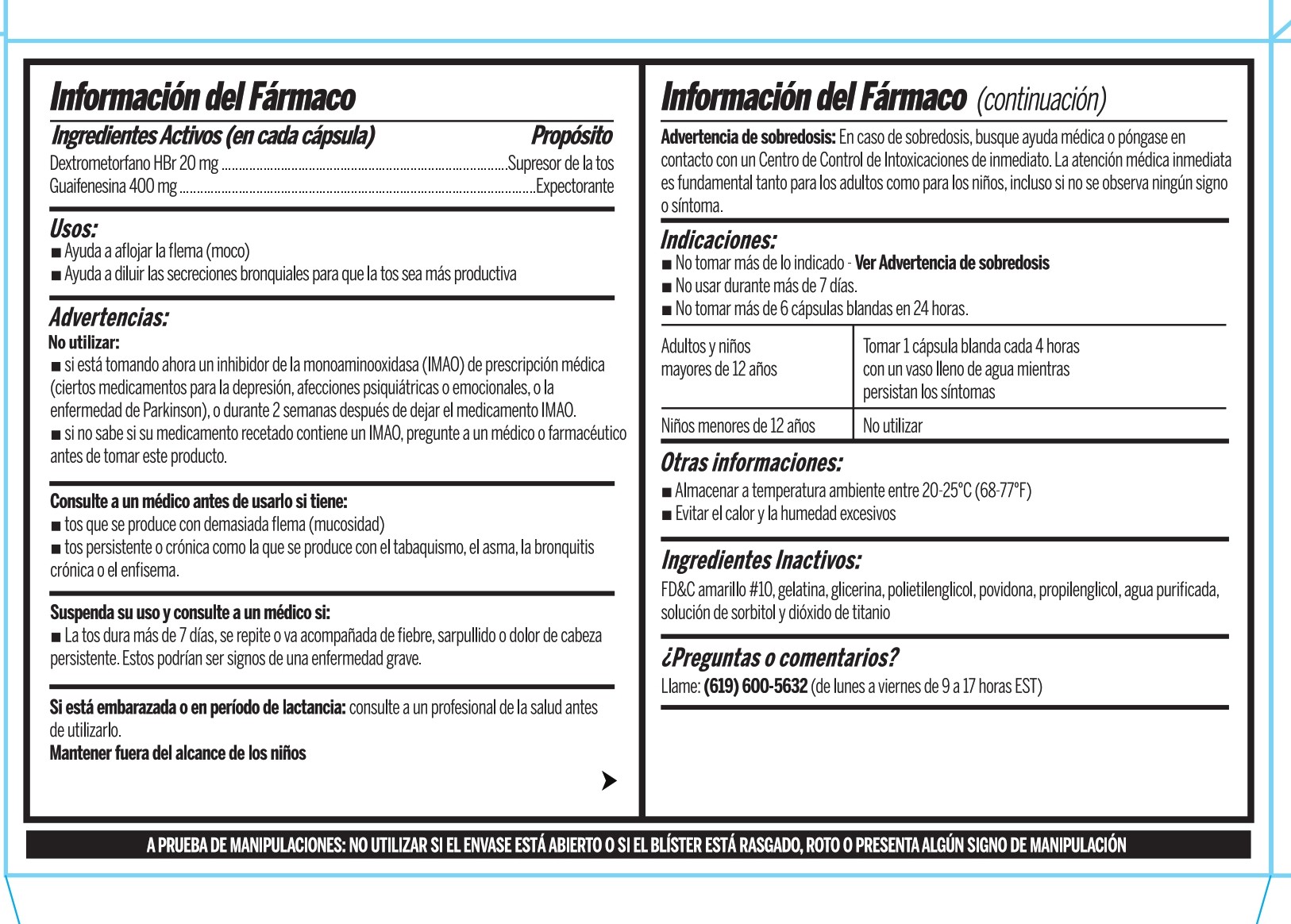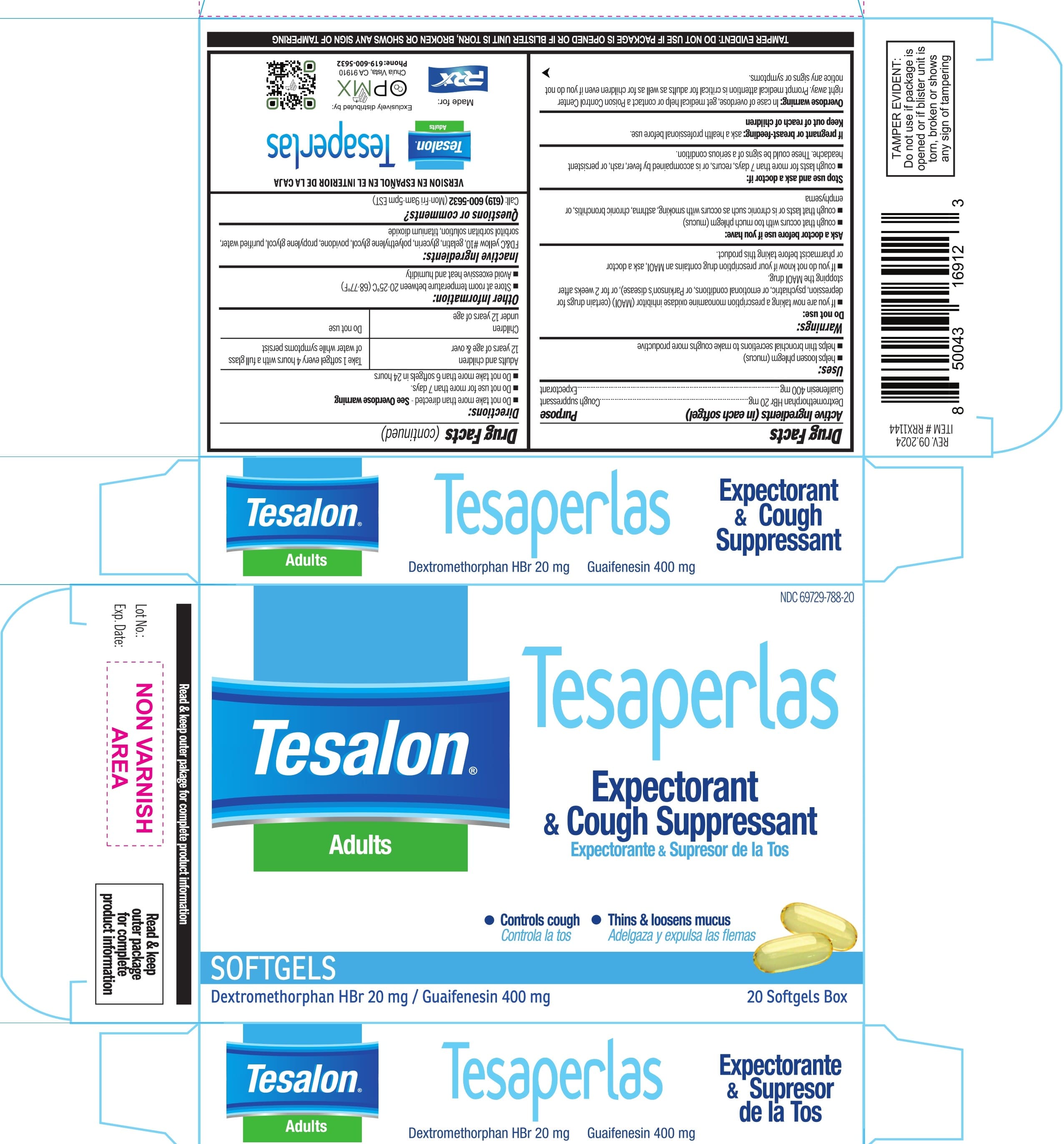 DRUG LABEL: TESALON Tesaperlas Severe Cold Max Relief
NDC: 69729-788 | Form: CAPSULE, LIQUID FILLED
Manufacturer: OPMX LLC
Category: otc | Type: HUMAN OTC DRUG LABEL
Date: 20260102

ACTIVE INGREDIENTS: DEXTROMETHORPHAN HYDROBROMIDE 20 mg/1 1; GUAIFENESIN 400 mg/1 1
INACTIVE INGREDIENTS: SORBITOL; SORBITAN; PROPYLENE GLYCOL; GELATIN; GLYCERIN; POVIDONE; POLYETHYLENE GLYCOL, UNSPECIFIED; WATER; D&C YELLOW NO. 10; TITANIUM DIOXIDE

TESALON Tesaperlas Severe Cold Max Relief

Active ingredients

Active Ingredients (in each softgel) | Purpose
Dextromethorphan HBr 20 mg | Cough suppressant
Guaifenesin 400 mg | Expectorant

Uses

- helps loosen phlegm (mucus)
- helps thin bronchial secretions to make coughs more productive

Warnings

Do not use:

- If you are now taking a prescription monoamine oxidase inhibitor (MAOI) (certain drugs for depression, psychiatric, or emotional conditions, or Parkison´s disease), or for 2 weeks after stopping the MAOI drug.
- If you do not know if your prescription drug contains an MAOI, ask a doctor or pharmacist before taking this product.

Ask a doctor before use if you have:

- cough that occurs with too much phlegm (mucus)
- cough that lasts or is chronic such as occurs with smoking, asthma, chronic bronchitis, or emphysema

Stop use and ask a doctor if:

- cough lasts more than 7 days, recurs, or is accompanied by fever, rash, or persistent headache. These could be signs of a serious condition.

If pregnant or breast-feeding:

- ask a health professional before use.

Overdose warning:

In case of overdose, get medical help or contact a Poison Control Center right away. Promt medical attention is critical for adults as well as for children even if you do not notice any signs or symptoms.

Directions:

- Do not take more than directed- See Overdose warning
- Do not use for more than 7 days.
- Do not take more than 6 softgels in 24 hours

DOSAGE AND ADMINISTRATION

Adults and children 12 years of age & over | Take 1 softgel every 4 hours with a full glass of water while symptoms persist
Children under 12 years of age | Do not use

Other information:

- Store at room temperature between 20-25°C (68-77°F)
- Avoid excessive heat and humidity

Inactive Ingredients:

FD&C yellow No. 10, gelatin, glycerin, polyethylene glycol, povidone, propylene glycol, purified water, sorbitol, sorbitan solution, titanium dioxide.

Questions or comments?

Call: (619) 600-5632 (Mon-Fri 9am-5pm EST)

PACKAGE LABEL

NDC 69729-788-20

Tesalon®

Tesaperlas

Adults

Expectorant & Cough Suppressant

Expectorante & Supresor de la Tos

Controls cough

Controla la tos

Thins & loosens mucus

Adelgaza y expulsa las flemas

SOFTGELS

Dextromethorphan HBr 20 mg / Guaifenesin 400 mg

20 Softgels Box

Read & keep package for complete product information

TAMPER EVIDENT; DO NOT USE IS PACKAGE IS OPENED OR IF BLISTER UNIT IS TORN, BROKEN OR SHOWS ANY SIGN OF TAMPERING